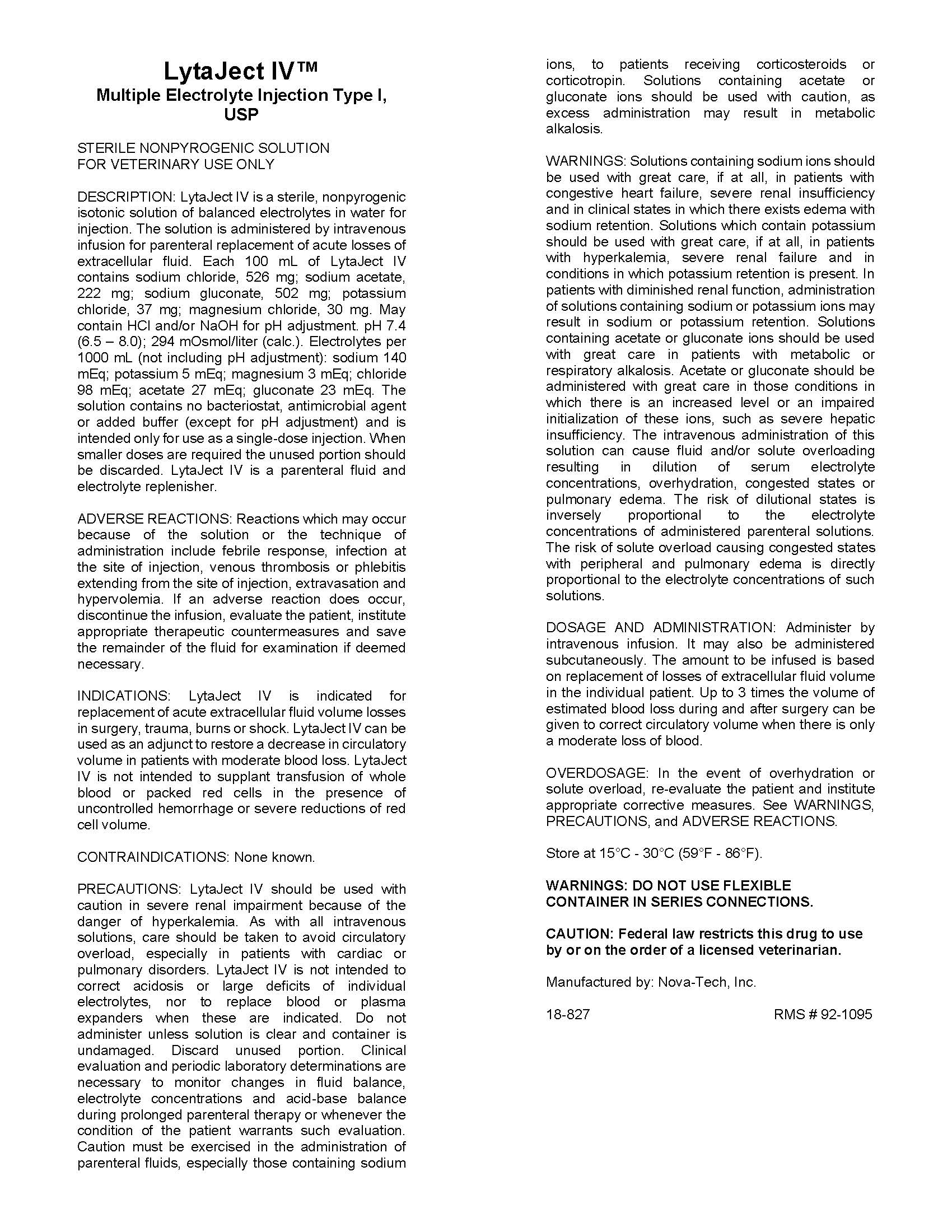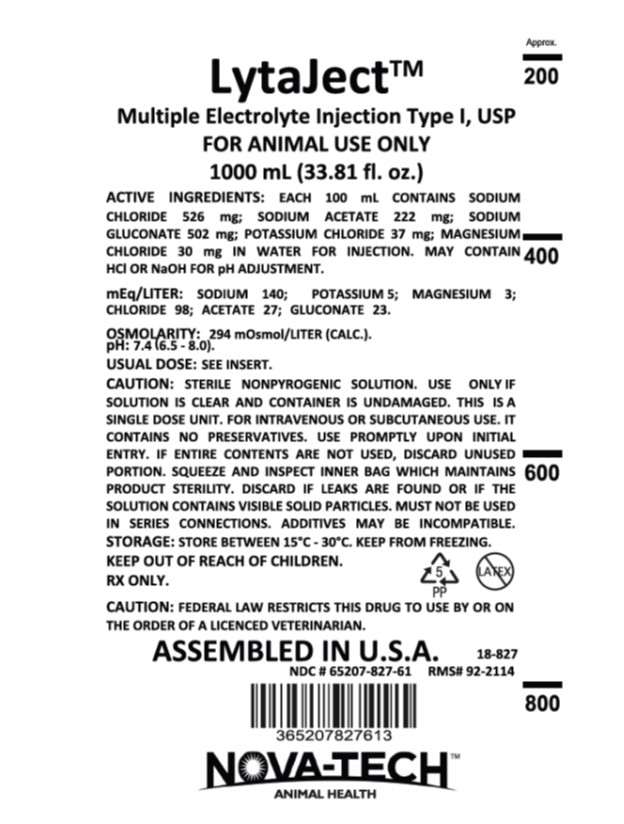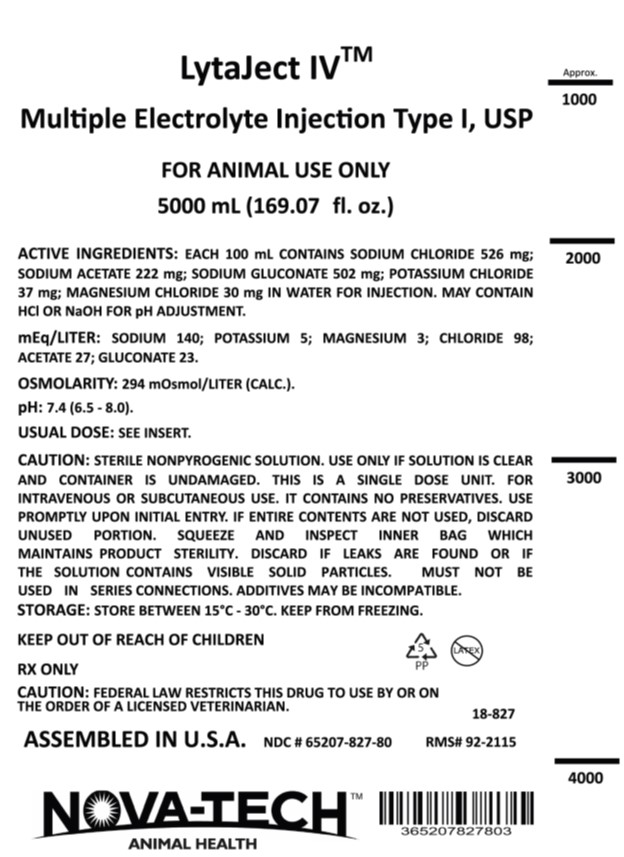 DRUG LABEL: LytaJect IV
NDC: 65207-827 | Form: INJECTION, SOLUTION
Manufacturer: Nova-Tech, Inc
Category: animal | Type: PRESCRIPTION ANIMAL DRUG LABEL
Date: 20250716

ACTIVE INGREDIENTS: SODIUM CHLORIDE 526 mg/100 mL; POTASSIUM CHLORIDE 37 mg/100 mL; MAGNESIUM CHLORIDE 30 1/100 mL; SODIUM ACETATE ANHYDROUS 222 1/100 mL; SODIUM GLUCONATE 502 1/100 mL

LytaJect IV

INFORMATION FOR OWNERS/CAREGIVERS

Assembled in U.S.A.

18-827

VETERINARY INDICATIONS

For animal use only

CAUTION:

Federal law restricts this drug to use by or on the order of a licensed veterinarian.

Active Ingredients:

Each 100 mL contains Sodium Chloride 526 mg; Sodium Acetate 222 mg; Sodium Gluconate 502 mg; Potassium Chloride 37 mg; Magnesium Chloride 30 mg in water for Injection. May contain HCl or NaOH for pH adjustment.

mEq/liter: Sodium 140; Potassium 5; Magnesium 3; Chloride 98; Acetate 27; Gluconate 23.

Osmolarity: 294 mOsmol/liter (calc).

pH: 7.4 (6.5 - 8.0).

CAUTION:

Sterile nonpyrogenic solution. Use only if solution is clear and container is undamaged. This is a single dose unit. For Intravenous or subcutaneous use. It contains no preservatives. Use promptly upon initial entry. If entire contents are not used, discard unused portion. Squeeze and inspect inner bag which maintains product sterility. Discard if leaks are found or if the solution contains visible solid particles. Must not be used in series connections. Additives may be incompatible.

Usual dose:

SEE INSERT.

STORAGE:

Store between 15°C - 30°C. Keep from freezing.

Description:

LytaJect IV is a sterile, nonpyrogenic isotonic solution of balanced electrolytes in water for injection. The solution is administered by intravenous infusion for parenteral replacement of acute losses of extracellular fluid. Each 100 mL of LytaJect IV contains sodium chloride, 526 mg; sodium acetate, 222 mg; sodium gluconate, 502 mg; potassium chloride, 37 mg; magnesium chloride, 30 mg. May contain HCl and/or NaOH for pH adjustment. pH 7.4 (6.5 - 8.0); 294 mOsmol/liter (calc.). Electrolytes per 1000 mL (not including pH adjustment): sodium 140 mEq; potassium 5 mEq; magnesium 3 mEq; chloride 98 mEq; acetate 27 mEq; gluconate 23 mEq. The solution contains no bacteriostat, antimicrobial agent or added buffer (except for pH adjustment) and is intended only for use as a single-dose injection. When smaller doses are required the unused portion should be discarded. LytaJect IV is a parenteral fluid and electrolyte replenisher.

Adverse Reactions:

Reactions which may occur because of the solution or the technique of administration include febrile response, infection at the site of injection, venous thrombosis or phlebitis extending from the site of injection, extravasation and hypervolemia. If an adverse reaction does occur, discontinue the infusion, evaluate the patient, institute appropriate therapeutic countermeasures and save the remainder of the fluid for examination if deemed necessary.

Indications:

LytaJect IV is indicated for replacement of acute extracellular fluid volume losses in surgery, trauma, burns or shock. JytaJect IV can be used as an adjunct to restore a decrease in circulatory volume in patients with moderate blood loss. lytaJect IV is not intended to supplant transfusion of whole blood or packed red cells in the presence of uncontrolled hemorrhage or severe reductions of red cell volume.

Contraindications:

None known.

Precautions:

LytaJect IV should be used with caution in severe renal impairment because of the danger of hyperkalemia. As with all intravenous solutions, care should be taken to avoid circulatory overload, especially in patients with cardiac or pulmonary disorders. LytaJect IV is not intended to correct acidosis or large deficits of individual electrolytes, nor to replace blood or plasma expanders when these are indicated. Do not administer unless solution is clear and container is undamaged. Discard unused portion. Clinical evaluation and periodic laboratory determinations are necessary to monitor changes in fluid balance, electrolyte concentrations and acid-base balance during prolonged parenteral therapy or whenever the condition of the patient warrants such evaluation. Caution must be exercised in the administration of parenteral fluids, especially those containing sodium ions, to patients receiving corticosteroids or corticotropin. Solutions containing acetate or gluconate ions should be used with caution, as excess administration may result in metabolic alkalosis.

Warnings:

Solutions containing sodium ions should be used with great care, if at all, in patients with congestive heart failure, severe renal insufficiency and in clinical states in which there exists edema with sodium retention. Solutions which contain potassium should be used with great care, if at all, in patients with hyperkalemia, severe renal failure and in conditions in which potassium retention is present. In patients with diminished renal function, administration of solutions containing sodium or potassium ions may result in sodium or potassium retention. Solutions containing acetate or gluconate ions should be used with great care in patients with metabolic or respiratory alkalosis. Acetate or gluconate should be administered with great care in those conditions in which there is an increased level or an impaired initialization of these ions, such as severe hepatic insufficiency. The intravenous administration of this solution can cause fluid and/or solute overloading resulting in dilution of serum electrolyte concentrations, overhydration, congested states or pulmonary edema. The risk of dilutional states is inversely proportional to the electrolyte concentrations of administered parenteral solutions. The risk if solute overload causing congested states with peripheral and pulmonary edema is directly proportional to the electrolyte concentrations of such solutions.

Dosage and Administration:

Administer by intravenous infusion. It may also be administered subcutaneously. The amount to be infused is based on replacement of losses of extracellular fluid volume in the individual patient. Up to 3 times the volume of estimated blood loss during and after surgery can be given to correct ciruculatory volume when there is only a moderate loss of blood.

Overdosage:

In the event of overhydration or solute overload, re-evaluate the patient and institute appropriate corrective measures. See WARNINGS, PRECAUTIONS, and ADVERSE REACTIONS.

INFORMATION FOR OWNERS/CAREGIVERS

Manufactured by: Nova-Tech, Inc.

Sterile nonpyrogenic solution. For veterinary use only.

Keep out of reach of children.